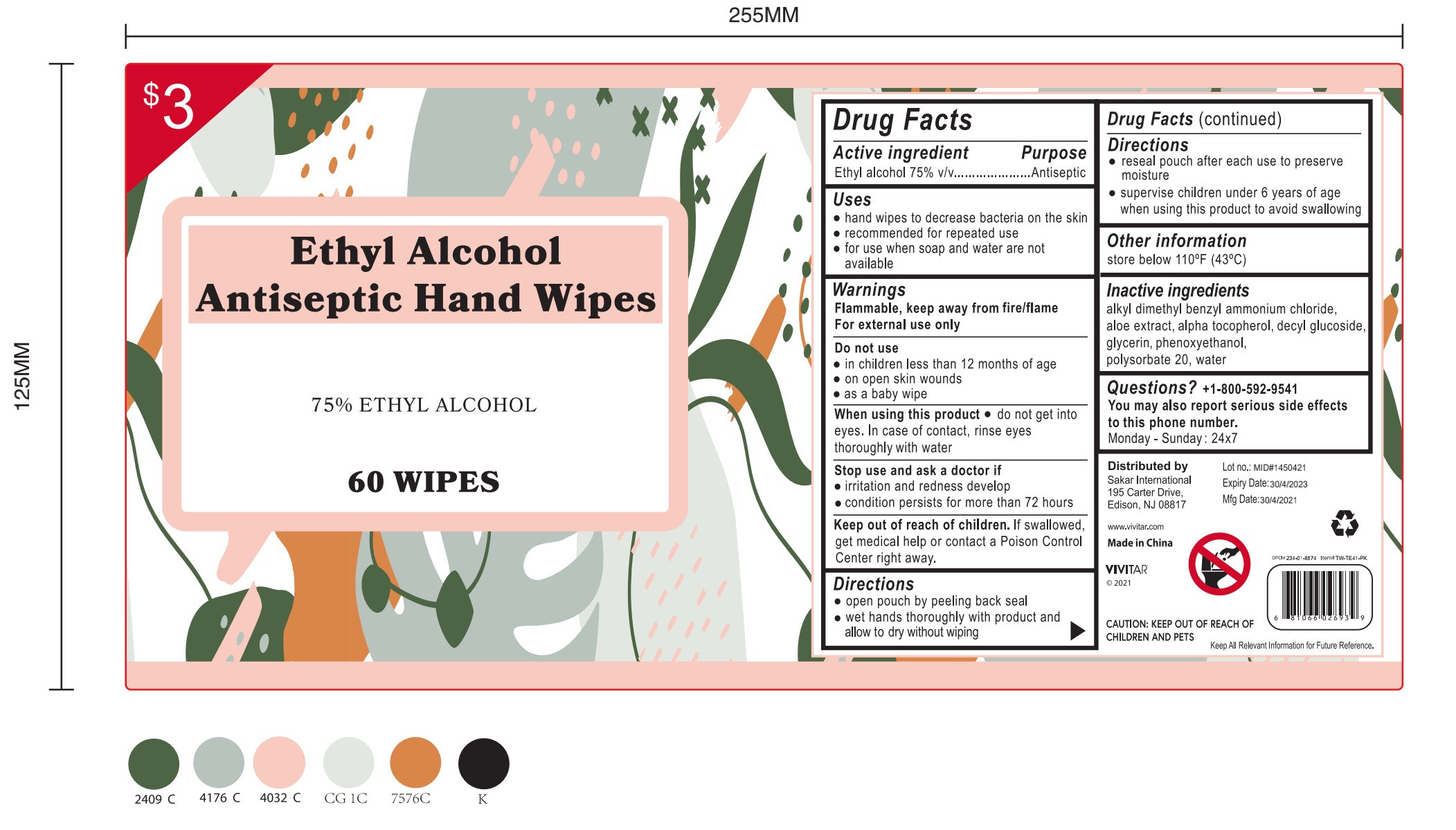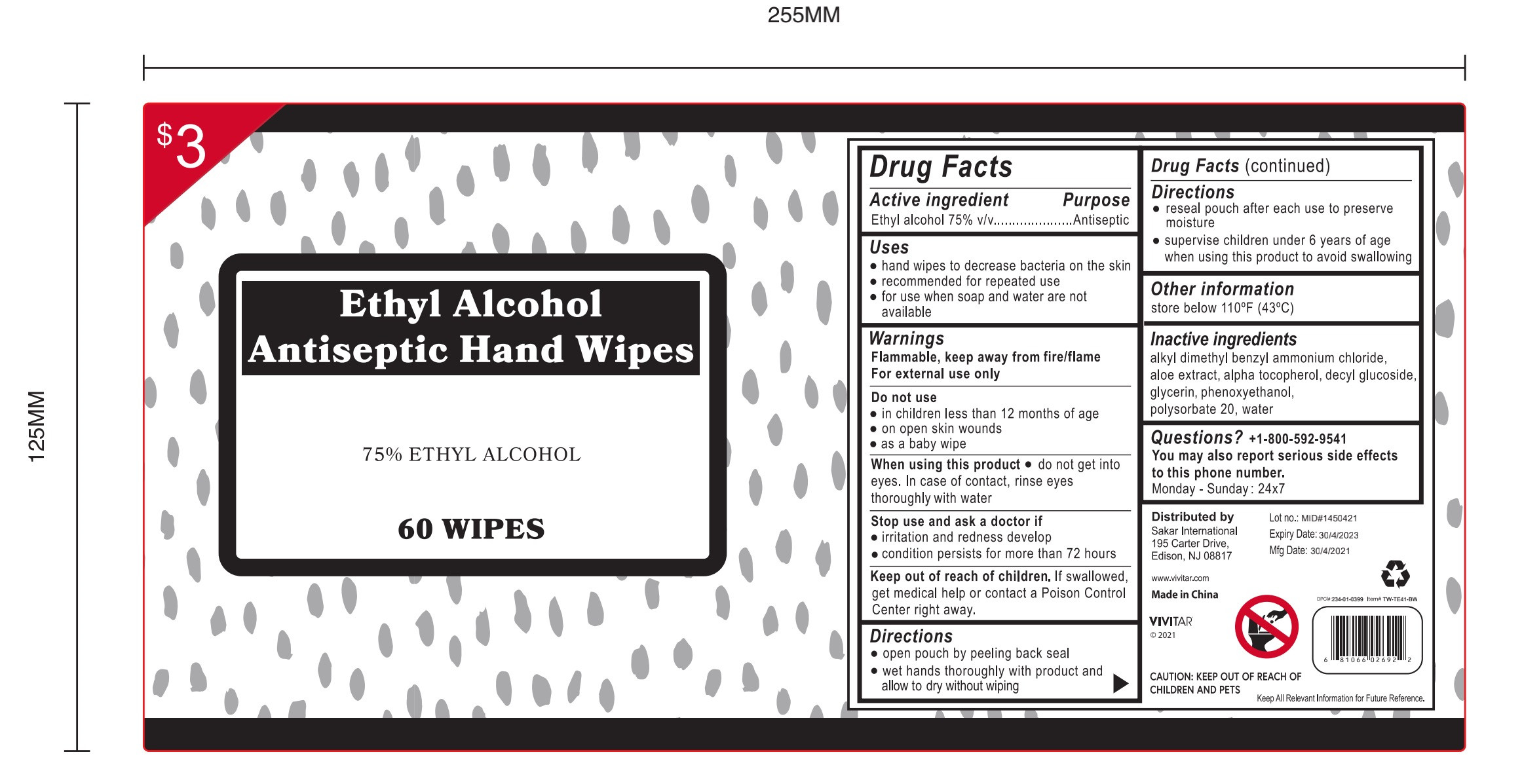 DRUG LABEL: Ethyl Alcohol Antiseptic Hand Wipes
NDC: 54826-006 | Form: CLOTH
Manufacturer: Cixi Fanhua Non Woven Products Co., Ltd
Category: otc | Type: HUMAN OTC DRUG LABEL
Date: 20210531

ACTIVE INGREDIENTS: ALCOHOL 75 mL/100 mL
INACTIVE INGREDIENTS: ALPHA-TOCOPHEROL; ALOE; BENZALKONIUM CHLORIDE; POLYSORBATE 20; WATER; GLYCERIN; DECYL GLUCOSIDE; PHENOXYETHANOL

ACTIVE INGREDIENT

Ethyl alcohol 75%

PURPOSE

Antiseptic

Directions

open pouch by peeling back seal
wet hands thoroughly with product andallow to dry without wiping

reseal pouch after each use to preservemoisture
supervise children under 6 years of agewhen using this product to avoid swallowing

INACTIVE INGREDIENT

Alkly dimethyl benzyl ammonium chloride

Aloe extract

Alpha tocopherol

Decyl glucoside

Glycerin

Phenoxyethanol

Polysorbate 20

water

Uses

hand wipes to decrease bacteria on the skin
recommended for repeated use
for use when soap and water are not available

WARNINGS

Flammable, keep away from fire/flame
For external use only

DO NOT USE

in children less than 12 months of age
on open skin wounds

as a baby wipe

When using this product . do not get into eyes. ln case of contact,rinse eyes thoroughly with water

Stop use and ask a doctor if. irritation and redness develop
condition persists for more than 72 hours

Keep out of reach of children. If swallowed,get medical help or contact a Poison ControlCenter right away.

Other information

store below 110°F(43°C)